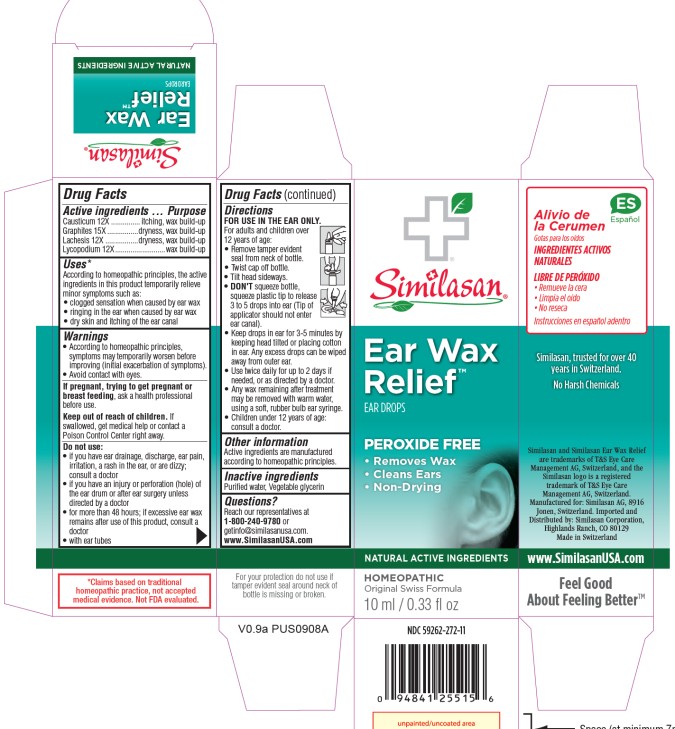 DRUG LABEL: Ear Wax Relief
NDC: 59262-272 | Form: SOLUTION
Manufacturer: Similasan Corporation
Category: homeopathic | Type: HUMAN OTC DRUG LABEL
Date: 20250410

ACTIVE INGREDIENTS: CAUSTICUM 12 [hp_X]/10 mL; GRAPHITE 15 [hp_X]/10 mL; LACHESIS MUTA VENOM 12 [hp_X]/10 mL; LYCOPODIUM CLAVATUM SPORE 12 [hp_X]/10 mL
INACTIVE INGREDIENTS: GLYCERIN

Ear Wax Relief

Active Ingredient

Causticum 12X

Purpose

itching, wax build-up

Active Ingredients

Graphites 15X

Purpose

dryness, wax build-up

Active Ingredient

Lachesis 12X

Purpose

dryness, wax build-up

Active Ingredient

Lycopodium 12X

Purpose

wax build-up

Uses:

According to homeopathic principles, the active ingredients in this product temporarily relieve minor symptoms such as:

- clogged sensation when caused by ear wax
- ringing in the ear when caused by ear wax
- dry skin and itching of the ear canal

Warnings:

- According to homeopathic principles, symptoms may temporarily worsen before improving (initial exacerbation of symptoms).
- Avoid contact with eyes.

If pregnant, trying to get pregnant or breast feeding,

ask a health professional before use.

Keep out of reach of children.

If swallowed, get medical help or contact a Poison Control Center right away.

Do not use:

- if you have ear drainage, discharge, ear pain, irritation, a rash in the ear, or are dizzy; consult a doctor
- if you have an injury or perforation (hole) of the ear drum or after ear surgery unless directed by a doctor
- for more than 48 hours; if excessive ear wax remains after the use of this product, consult a doctor
- with ear tubes

Directions:

FOR USE IN THE EAR ONLY.

For adults and children, over 12 years of age:

- Remove tamper evident seal from neck of bottle.
- Twist cap off bottle.
- Tilt head sideways, squeeze plastic applicator to release 2-3 drops into ear. (Tip of applicator should not enter ear canal).
- Keep drops in ear for 3-5 minutes by keeping head tilted or placing cotton in ear. Any excess drops can be wiped away from outer ear.
- Use twice daily for up to 2 days if needed, or as directed by a doctor.
- Any wax remaining after treatment may be removed by with warm water, using a soft, rubber bulb ear syringe.
- Children under 12 years of age: consult a doctor.

Other information:

Active ingredients are manufactured according to homeopathic principles.

Inactive ingredient:

Vegetable glycerin

Questions?

Reach our representatives at: 1-800-240-9780 or getinfo@similasanusa.com
www.SimilasanUSA.com

Principle Display Panel

NDC 59262-272-11
Similasan
Ear Wax Relief
EAR DROPS
10 ml / 0.33 fl oz